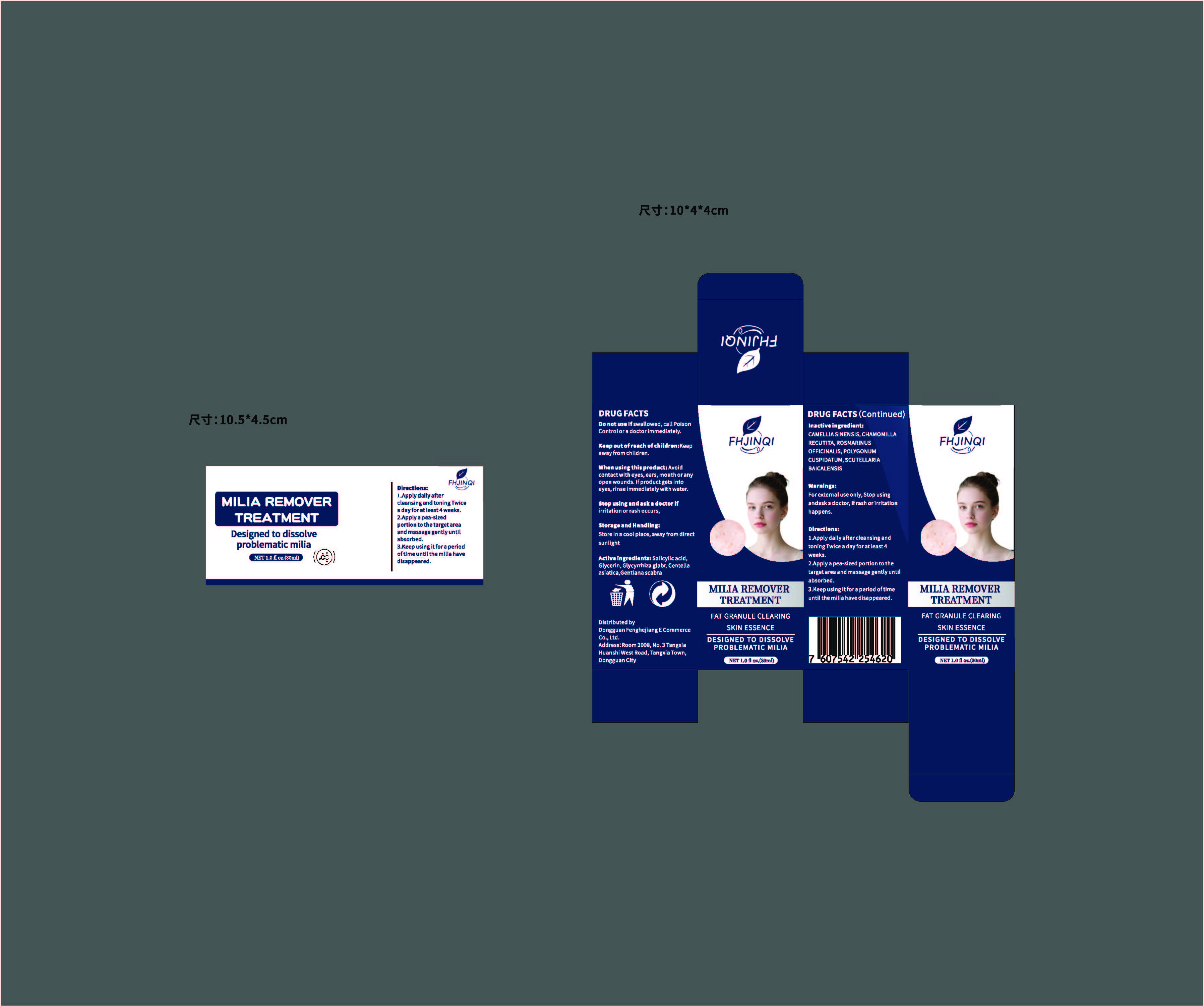 DRUG LABEL: Milia remover treatment
NDC: 85960-001 | Form: CREAM
Manufacturer: Dongguan Fenghejiang E Commerce Co., Ltd.
Category: otc | Type: HUMAN OTC DRUG LABEL
Date: 20250727

ACTIVE INGREDIENTS: GENTIANA SCABRA ROOT 1 g/100 mL; CENTELLA ASIATICA 2 g/100 mL; GLYCERIN 3 g/100 mL; GLYCYRRHIZA GLABRA LEAF 0.5 g/100 mL; SALICYLIC ACID 0.8 g/100 mL
INACTIVE INGREDIENTS: ROSMARINUS OFFICINALIS (ROSEMARY) LEAF POWDER; SCUTELLARIA BAICALENSIS ROOT; CAMELLIA SINENSIS ROOT; MATRICARIA RECUTITA LEAF; POLYGONUM CUSPIDATUM LEAF

ACTIVE INGREDIENT

GENTIANA SCABRA 1%

CENTELLA ASIATICA、2%

Glycerin,3%

Glycyrrhiza glabr0.5%

salicylic acid 0.8%

PURPOSE

FAT GRANULE CLEARING
SKIN ESSENCEDESIGNED TO DISSOLVEPROBLEMATIC MILIA

WHEN USING

When usingthis product: Avoidcontact with eyes,ears, mouth or anyopen wounds.lf product getsintoeyes, rinseimmediately with water.

WARNINGS

Warnings:Forexternal use only, Stop usingandask a doctor, ifrash orirritationhappens.

Keep out ofreach ofchildren:Keepaway from children.

Directions:
1.Apply daily after cleansingandtoning Twice a day for at least 4weeks.2.Apply a pea-sized portion to thetarget area and massage gentlyuntilabsorbed.3.Keep usingit fora period oftimeuntil the milia have disappeared.

Directions:
1.Apply daily after cleansingandtoning Twice a day for at least 4weeks.2.Apply a pea-sized portion to thetarget area and massage gentlyuntilabsorbed.3.Keep usingit fora period oftimeuntil the milia have disappeared.

OTHER SAFETY INFORMATION

Storage and Handling:Store in a cool place, away from directsunlight

Inactive ingredient:
CAMELLIASINENSIS,CHAMOMILLARECUTITA,ROSMARINUSOFFICINALIS,POLYGONUMCUSPIDATUM,SCUTELLARIA
BAICALENSIS